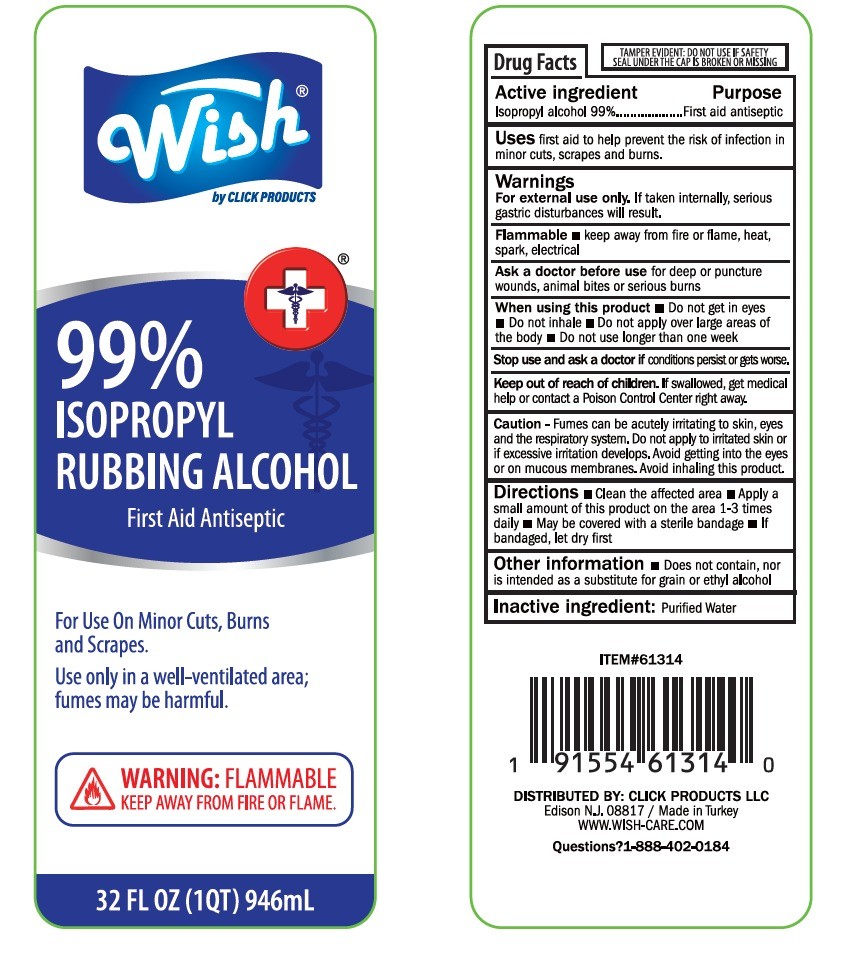 DRUG LABEL: WISH ISOPROPYL ALCOHOL
NDC: 71611-083 | Form: LIQUID
Manufacturer: Click Products LLC
Category: otc | Type: HUMAN OTC DRUG LABEL
Date: 20260113

ACTIVE INGREDIENTS: ISOPROPYL ALCOHOL 936 mL/946 mL
INACTIVE INGREDIENTS: WATER 9.46 mL/946 mL

DOSAGE AND ADMINISTRATION

Directions

Clean the affected area

Apply a small amount of this product on the area 1-3 times daily

May be covered with a sterile bandage

If bandaged, let dry first

WARNINGS

For external use only

If taken internally, serious gastric disturbances will result

Flammable

Keep away from fire or flame, heat, spark, electrical

Keep out of reach of children. If swallowed, get medical hgelp or contact a Poison Control Center right away

ACTIVE INGREDIENT

Isopropyl alcohol 99%

PURPOSE

First aid antiseptic

INDICATIONS AND USAGE

Uses

First aid to help prevent the risk of infection in minor cuts, scrapes and burns

INACTIVE INGREDIENT

Purified Water